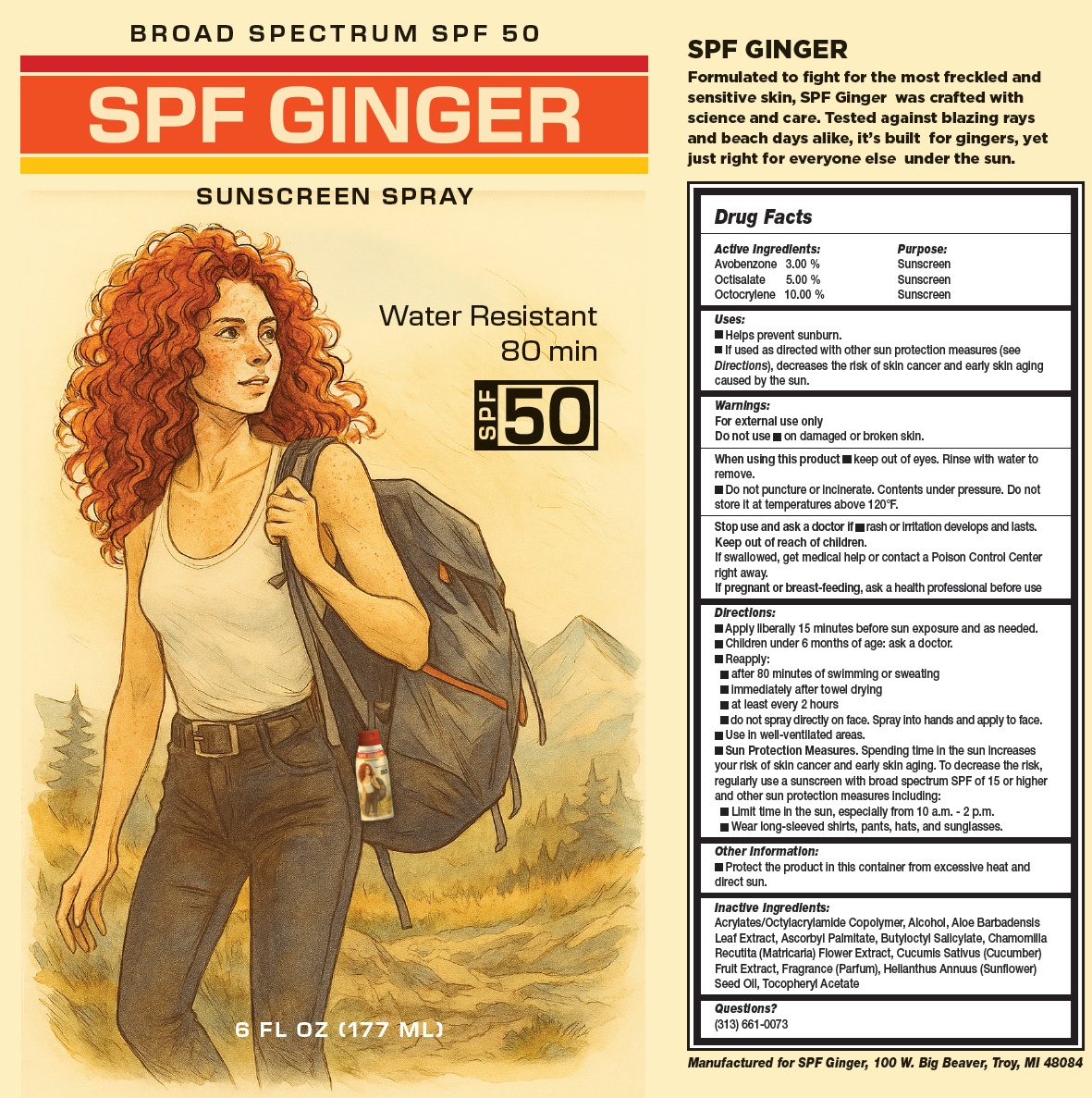 DRUG LABEL: SPF Ginger Sunscreen SPF 50
NDC: 87341-928 | Form: LIQUID
Manufacturer: SPF GINGER LLC
Category: otc | Type: HUMAN OTC DRUG LABEL
Date: 20260126

ACTIVE INGREDIENTS: AVOBENZONE 30 mg/1 mL; OCTISALATE 50 mg/1 mL; OCTOCRYLENE 100 mg/1 mL
INACTIVE INGREDIENTS: ALCOHOL; ALOE VERA LEAF; ASCORBYL PALMITATE; BUTYLOCTYL SALICYLATE; CHAMOMILE; CUCUMBER; SUNFLOWER OIL; .ALPHA.-TOCOPHEROL ACETATE

SPF Ginger Sunscreen Spray SPF 50

Active Ingredients:

Avobenzone 3.00 %

Octisalate 5.00 %

Octocrylene 10.00 %

Purpose:

Sunscreen

Uses:

- Helps prevent sunburn
- If used as directed with other sun protection measures (see Directions), decreases the risk of skin cancer and early skin aging caused by the sun.

Warnings:

For external use only

Do not use

- on damaged or broken skin.

When using this product

- keep out of eyes. Rinse with water to remove.
- Do not puncture or incinerate. Contents under pressure. Do not store it at temperatures above 120°F.

Stop use and ask a doctor if

- rash or irritation develops and lasts.

Keep out of reach of children.

If swallowed, get medical help or contact a Poison Control Center right away.

If pregnant or breast-feeding,

ask a health professional before use

Directions:

- Apply liberally 15 minutes before sun exposure and as needed.
- Children under 6 months of age: ask a doctor
- Reapply:
- after 80 minutes of swimming or sweating
- immediately after towel drying
- at least every 2 hours
- do not spray directly on face. Spray into hands and apply to face.
- Use in well-ventilated areas
- Sun Protection Measures.Spending time in the sun increases your risk of skin cancer and early skin aging. To decrease the risk, regularly use a sunscreen with broad spectrum SPF of 15 or higher and other sun protection measures including:
- Limit time in the sun, especially from 10 a.m. - 2 p.m.
- Wear long-sleeved shirts, pants, hats, and sunglasses.

Other Information

- Protect the product in this container from excessive heat and direct sun.

Inactive Ingredients:

Acrylates/Octylacrylamide Copolymer, Alcohol, Aloe Barbadensis Leaf Extract, Ascorbyl Palmitate, Butyloctyl Salicylate, Chamomilla Recutita (Matricaria) Flower Extract, Cucumis Sativus (Cucumber) Fruit Extract, Fragrance (Parfum), Helianthus Annuus (Sunflower) Seed Oil,Tocopheryl Acetate

Questions?

(313) 661-0073